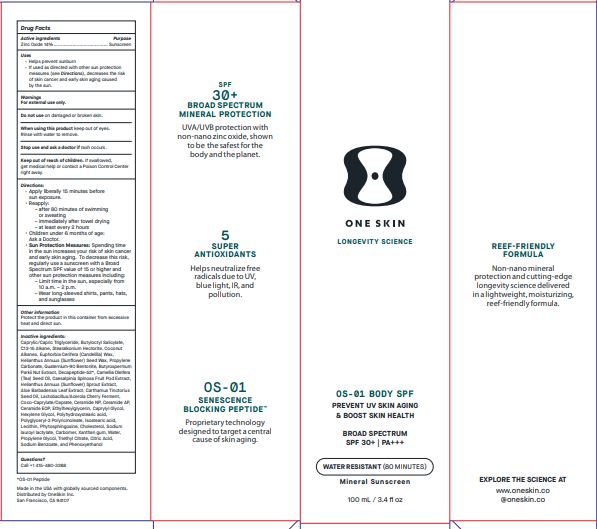 DRUG LABEL: OS-01 Body SPF 30
NDC: 84451-001 | Form: CREAM
Manufacturer: ONESKIN, INC
Category: otc | Type: HUMAN OTC DRUG LABEL
Date: 20240830

ACTIVE INGREDIENTS: ZINC OXIDE 14 g/100 g
INACTIVE INGREDIENTS: BIFIDOBACTERIUM ANIMALIS LACTIS; CANDELILLA WAX; CARBOMER HOMOPOLYMER, UNSPECIFIED TYPE; SHEANUT; PHYTOSPHINGOSINE; SODIUM BENZOATE; PHENOXYETHANOL; CAESALPINIA SPINOSA FRUIT POD; SAFFLOWER OIL; MEDIUM-CHAIN TRIGLYCERIDES; POLYGLYCERYL-3 PENTARICINOLEATE; BUTYLOCTYL SALICYLATE; HELIANTHUS ANNUUS SEED WAX; SODIUM LAUROYL LACTYLATE; HELIANTHUS ANNUUS SPROUT; ISOSTEARIC ACID; LECITHIN, SOYBEAN; STEARALKONIUM HECTORITE; QUATERNIUM-90 BENTONITE; CAMELLIA OIL; ALOE VERA LEAF; MALPIGHIA EMARGINATA SEED; CERAMIDE NP; CERAMIDE AP; POLYHYDROXYSTEARIC ACID (2300 MW); CHOLESTEROL; XANTHAN GUM; CITRIC ACID MONOHYDRATE; TRIETHYL CITRATE; C13-15 ALKANE; COCONUT ALKANES; COCO-CAPRYLATE/CAPRATE; HEXYLENE GLYCOL; PROPYLENE GLYCOL; PROPYLENE CARBONATE; ETHYLHEXYLGLYCERIN; CAPRYLYL GLYCOL; WATER

Drug Facts

Active ingredients – Zinc Oxide 14 %

Purpose – Sunscreen

Uses –

Helps prevent sunburn
If used as directed with other sun protection measures (See direction), decreases the risk of skin cancer and early skin aging caused by the sun.

WARNINGS

Warning – For external use only

Do not use on damaged or broken skin

When using this product keep out of eye. Rinse with water to remove.

Stop use and ask doctor if rash occurs.

Keep out of reach of children. If swallowed, get medical help or contact a poison control center right away.

DOSAGE AND ADMINISTRATION

Direction-

Apply liberally 15 minutes before sun exposure.
Reapply after 80 minutes of swimming or sweating.
immediately after towel drying, at least every 2 hours
Children under 6 months of age: Ask a doctor.
Sun protection measures: spending time in the sun increases your risk of skin cancer and early skin aging. To decrease the risk, regularly use a sunscreen with a broad-spectrum value of 15 or higher and other sun protection measures including:
Limit time in the sun. especially from 10 am to 2 pm
Wear long-sleeved shirts, pants hats and sunglasses.

OTHER SAFETY INFORMATION

Protect the product in this container from excessive heat and direct sun.

INACTIVE INGREDIENT

Inactive Ingredients: Caprylic/Capric Triglyceride 40 - 65 Butyloctyl Salicylate, C13-15 Alkane, Stearalkonium Hectorite,Coconut Alkanes, Euphorbia Cerifera (Candelilla) Wax, Helianthus Annuus (Sunflower) Seed Wax, Propylene Carbonate, Quaternium-90 Bentonite, Butyrospermum Parkii Nut Extract, Decapeptide-52, Camellia Oleifera (Tea) Seed Oil, Caesalpinia Spinosa Fruit Pod Extract, Helianthus Annuus (Sunflower) Sprout Extract, Aloe Barbadensis Leaf Extract, Carthamus Tinctorius Seed Oil, Lactobacillus/Acerola Cherry Ferment, Coco-Caprylate/Caprate, Ceramide NP, Ceramide AP, Ceramide EOP, Ethylhexylglycerin, Caprylyl Glycol, Hexylene Glycol, Polyhydroxystearic acid, Polyglyceryl-3 Polyricinoleate, Isostearic acid, Lecithin, Phytosphingosine, Cholesterol, Sodium lauroyl lactylate , Carbomer, Xanthan gum, Water, Propylene Glycol ,Triethyl Citrate, Citric Acid, Sodium Benzoate, Phenoxyethanol.